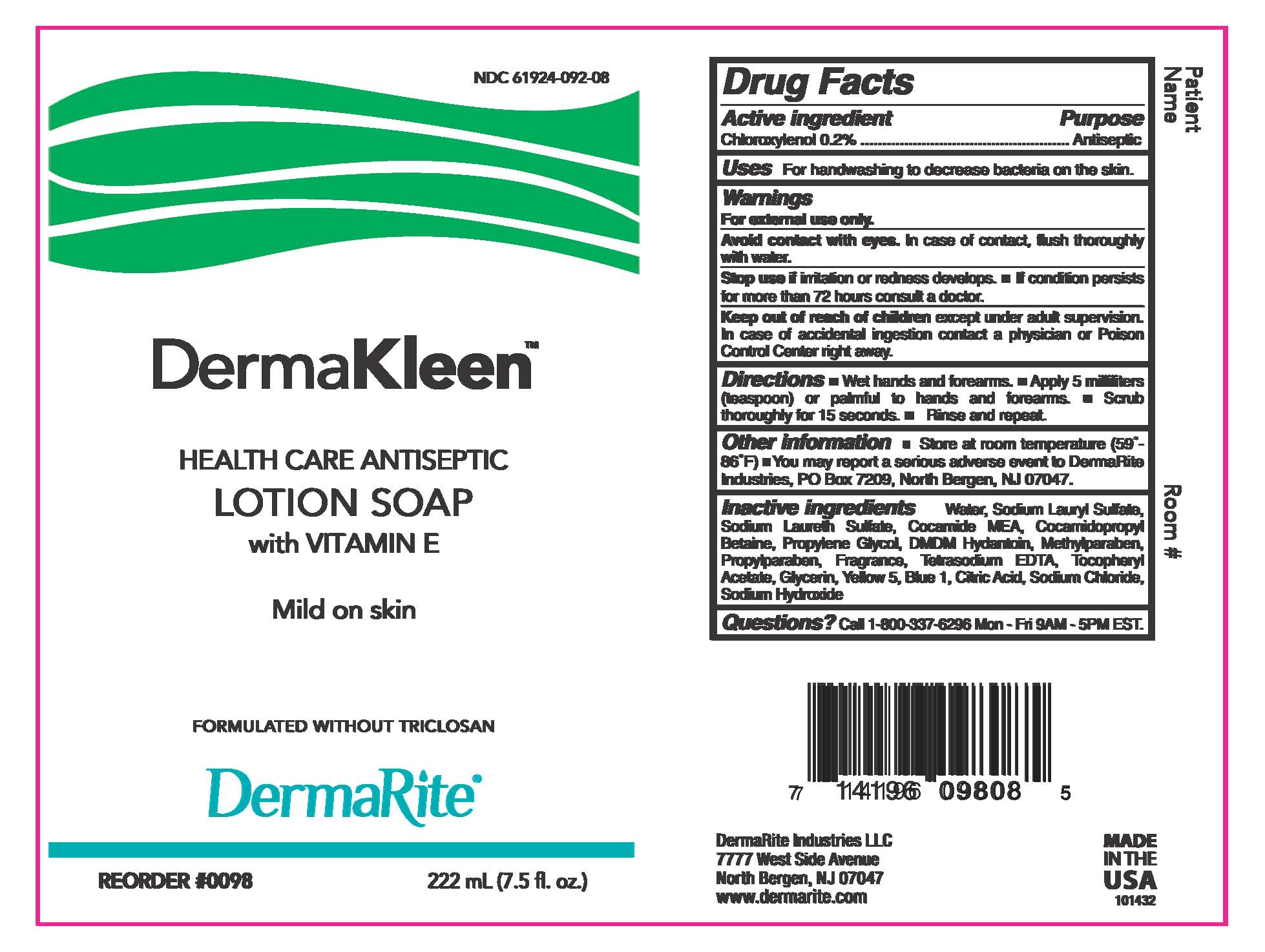 DRUG LABEL: DERMAKLEEN
NDC: 61924-092 | Form: SOAP
Manufacturer: Dermarite Industries LLC
Category: otc | Type: HUMAN OTC DRUG LABEL
Date: 20241205

ACTIVE INGREDIENTS: CHLOROXYLENOL 0.002 g/1 mL
INACTIVE INGREDIENTS: COCO MONOETHANOLAMIDE; COCAMIDOPROPYL BETAINE; METHYLCHLOROISOTHIAZOLINONE; METHYLISOTHIAZOLINONE; SODIUM LAURETH SULFATE; SODIUM LAURYL SULFATE; PROPYLENE GLYCOL; DMDM HYDANTOIN; METHYLPARABEN; PROPYLPARABEN; EDETATE SODIUM; SODIUM HYDROXIDE; GLYCERIN; .ALPHA.-TOCOPHEROL ACETATE; D&C GREEN NO. 6; WATER; CITRIC ACID MONOHYDRATE; SODIUM CHLORIDE

DRUG LISTING: DERMAKLEEN

Active Ingredient:

Chloroxylenol 0.2%

Purpose:

Antimicrobial

Uses:

For handwashing to decrease bacteria on the skin.

Warnings

- For external use only.
- Avoid contact with eyes. In case of contact, flush thoroughly with water.
- Stop use and ask a doctor if irritation or redness develops.

Warnings

- Keep out of children's reach except under adult supervision. In case of accidental ingestion contact a physician or Poison Control Center rightaway.

Directions:

- Dispense into hands, wet as needed.
- Lather vigorously for at least 15 seconds
- Wash skin, rinse thoroughly and dry.

Inactive Ingredients:

Cocamide MEA, Cocamidoproplyl Betaine, Citric Acid, DMDM Hydantoin, D&C Green#6, Fragrance, Glycerin, Methylchloroisothiazolinone, Methylparaben, Methylisothiazolinone, Propylene Glycol, Propylparaben, Sodium Chloride, Sodium Hydroxide, Sodium Laureth Sulfate, Sodium Lauryl Sulfate, Tetrasodium EDTA, Tocopheryl Acetate, Water.

Questions?

Call 1-800-337-6296